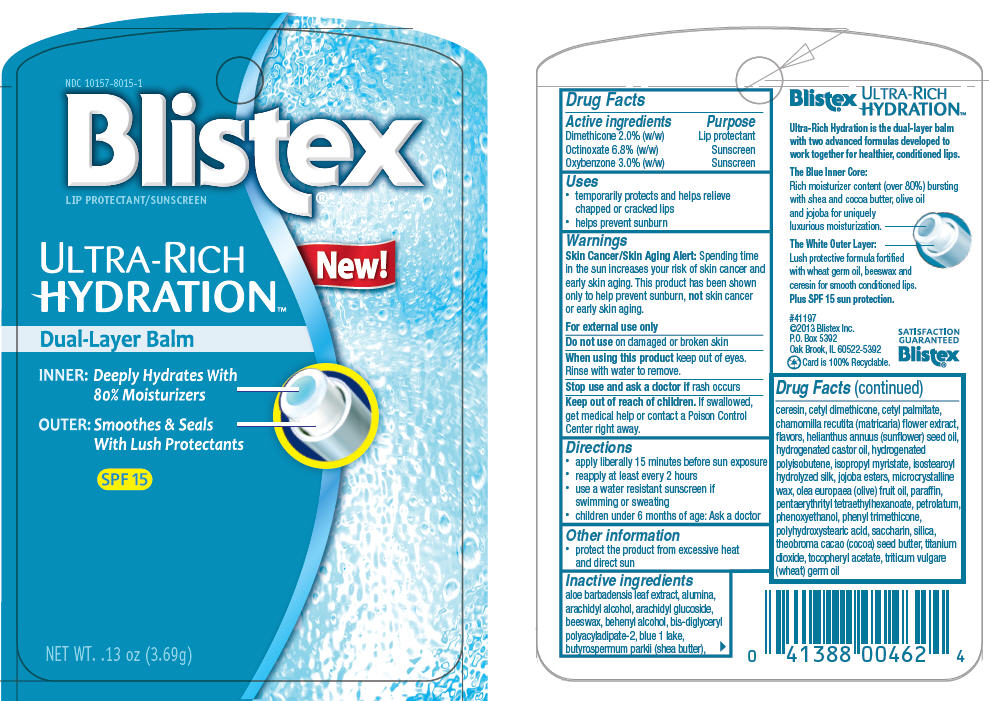 DRUG LABEL: Blistex 
NDC: 10157-8015 | Form: STICK
Manufacturer: Blistex Inc.
Category: otc | Type: HUMAN OTC DRUG LABEL
Date: 20140416

ACTIVE INGREDIENTS: Octinoxate 6.8 g/100 g; Oxybenzone 3 g/100 g; Dimethicone 2 g/100 g
INACTIVE INGREDIENTS: yellow wax; PENTAERYTHRITYL TETRAETHYLHEXANOATE; PETROLATUM; PARAFFIN; HYDROGENATED CASTOR OIL; microcrystalline wax; ISOPROPYL MYRISTATE; TITANIUM DIOXIDE; SHEA BUTTER; ALUMINUM OXIDE; SILICON DIOXIDE; CETYL PALMITATE; ARACHIDYL ALCOHOL; DOCOSANOL; ARACHIDYL GLUCOSIDE; OLIVE OIL; ALOE VERA LEAF; .ALPHA.-TOCOPHEROL ACETATE; WHEAT GERM OIL; PHENYL TRIMETHICONE; SUNFLOWER OIL; CHAMOMILE; ceresin; COCOA BUTTER; SACCHARIN; FD&C BLUE NO. 1; PHENOXYETHANOL

Blistex®
Ultra-Rich Hydration™

Drug Facts

ACTIVE INGREDIENT

Active ingredients | Purpose
Dimethicone 2.0% (w/w) | Lip protectant
Octinoxate 6.8% (w/w) | Sunscreen
Oxybenzone 3.0% (w/w) | Sunscreen

Uses

- temporarily protects and helps relieve chapped or cracked lips
- helps prevent sunburn

Warnings

Skin Cancer/Skin Aging Alert

Spending time in the sun increases your risk of skin cancer and early skin aging. This product has been shown only to help prevent sunburn, not skin cancer or early skin aging.

For external use only

Do not use on damaged or broken skin

When using this product keep out of eyes. Rinse with water to remove.

Stop use and ask a doctor if rash occurs

Keep out of reach of children. If swallowed, get medical help or contact a Poison Control Center right away.

Directions

- apply liberally 15 minutes before sun exposure
- reapply at least every 2 hours
- use a water resistant sunscreen if swimming or sweating
- children under 6 months of age: Ask a doctor

Other information

- protect the product from excessive heat and direct sun

Inactive ingredients

aloe barbadensis leaf extract, alumina, arachidyl alcohol, arachidyl glucoside, beeswax, behenyl alcohol, bis-diglyceryl polyacyladipate-2, blue 1 lake, butyrospermum parkii (shea butter), ceresin, cetyl dimethicone, cetyl palmitate, chamomilla recutita (matricaria) flower extract, flavors, helianthus annuus (sunflower) seed oil, hydrogenated castor oil, hydrogenated polyisobutene, isopropyl myristate, isostearoyl hydrolyzed silk, jojoba esters, microcrystalline wax, olea europaea (olive) fruit oil, paraffin, pentaerythrityl tetraethylhexanoate, petrolatum, phenoxyethanol, phenyl trimethicone, polyhydroxystearic acid, saccharin, silica, theobroma cacao (cocoa) seed butter, titanium dioxide, tocopheryl acetate, triticum vulgare (wheat) germ oil

PRINCIPAL DISPLAY PANEL - 3.69 g Cylinder Blister Pack

NDC 10157-8015-1
Blistex®
LIP PROTECTANT/SUNSCREEN

ULTRA-RICH
HYDRATION™

NEW!

Dual-Layer Balm

INNER: Deeply Hydrates With
80% Moisturizers

OUTER: Smoothes & Seals
With Lush Protectants

SPF 15

NET WT. .13 oz (3.69g)